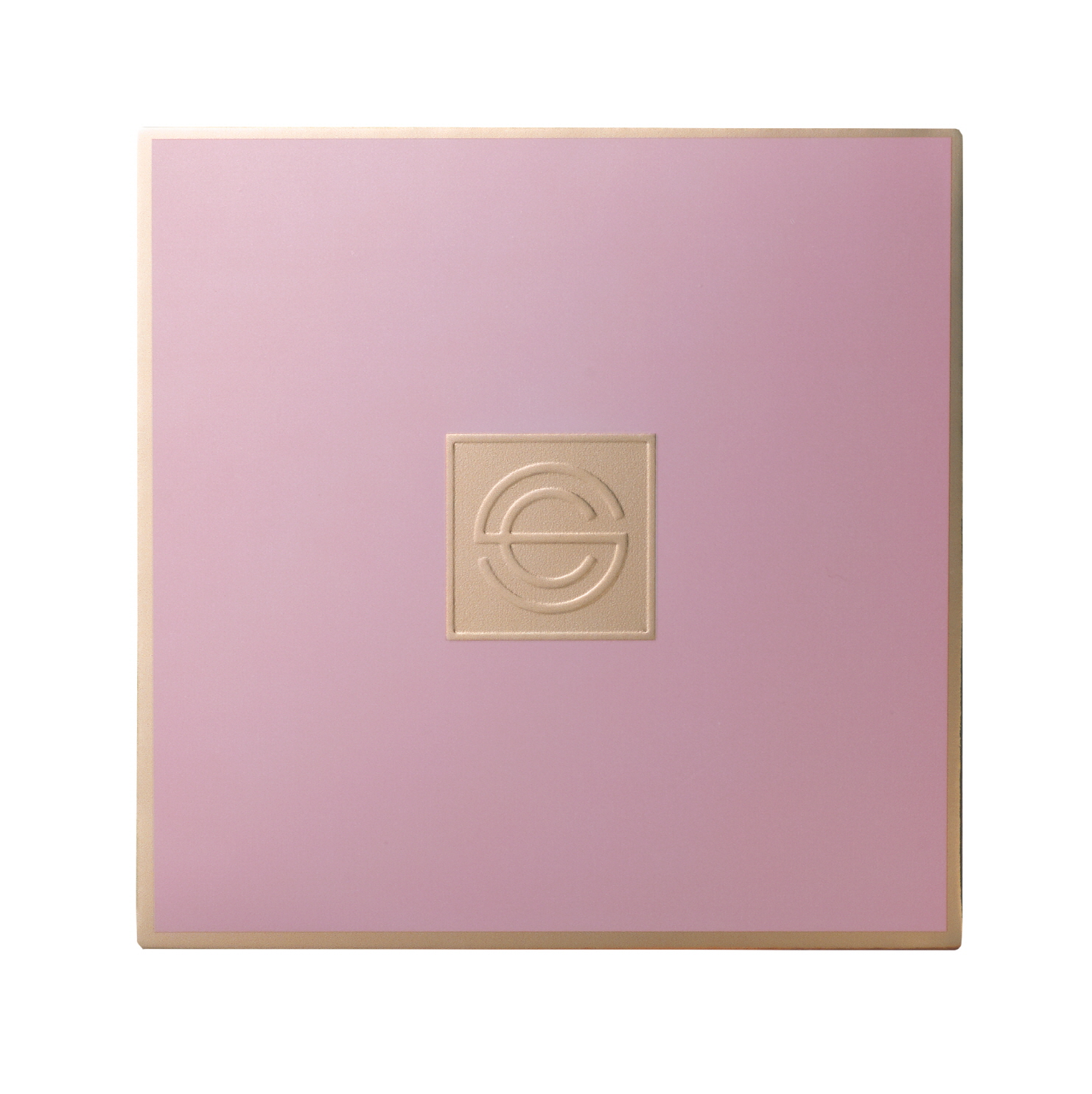 DRUG LABEL: DPC PINK AURA CUSHION NO.23
NDC: 71673-0008 | Form: LIQUID
Manufacturer: MSCO
Category: otc | Type: HUMAN OTC DRUG LABEL
Date: 20170824

ACTIVE INGREDIENTS: OCTINOXATE 7 g/100 g; AMILOXATE 3 g/100 g; OCTISALATE 3 g/100 g; BEMOTRIZINOL 1.5 g/100 g; TITANIUM DIOXIDE 12.7 g/100 g
INACTIVE INGREDIENTS: WATER

ACTIVE INGREDIENT

Titanium Dioxide, Ethylhexyl Methoxycinnamate, Ethylhexyl Salicylate, Isoamyl p-Methoxycinnamate, Bis-Ethylhexyloxyphenol Methoxyphenyl Triazine, Adenosine

INACTIVE INGREDIENT

Water, Butylene Glycol, etc.

PURPOSE

Sun block, Skin whitening, Wrinkle reducer

keep out or reach of the children

INDICATIONS AND USAGE

Take the puff and press it into the cushion, then tap it all round your face to spread it evenly on your face.

WARNINGS

For external use only.
Avoid contact with eyes. Not for human consumption.
Discontinue use if irritation occurs.
If irritation persists, consult a physician.
Please close the lid after use. If not, useful moisurizing and other contents can vaporize and the content can be ruduced.

DOSAGE AND ADMINISTRATION

for external use only